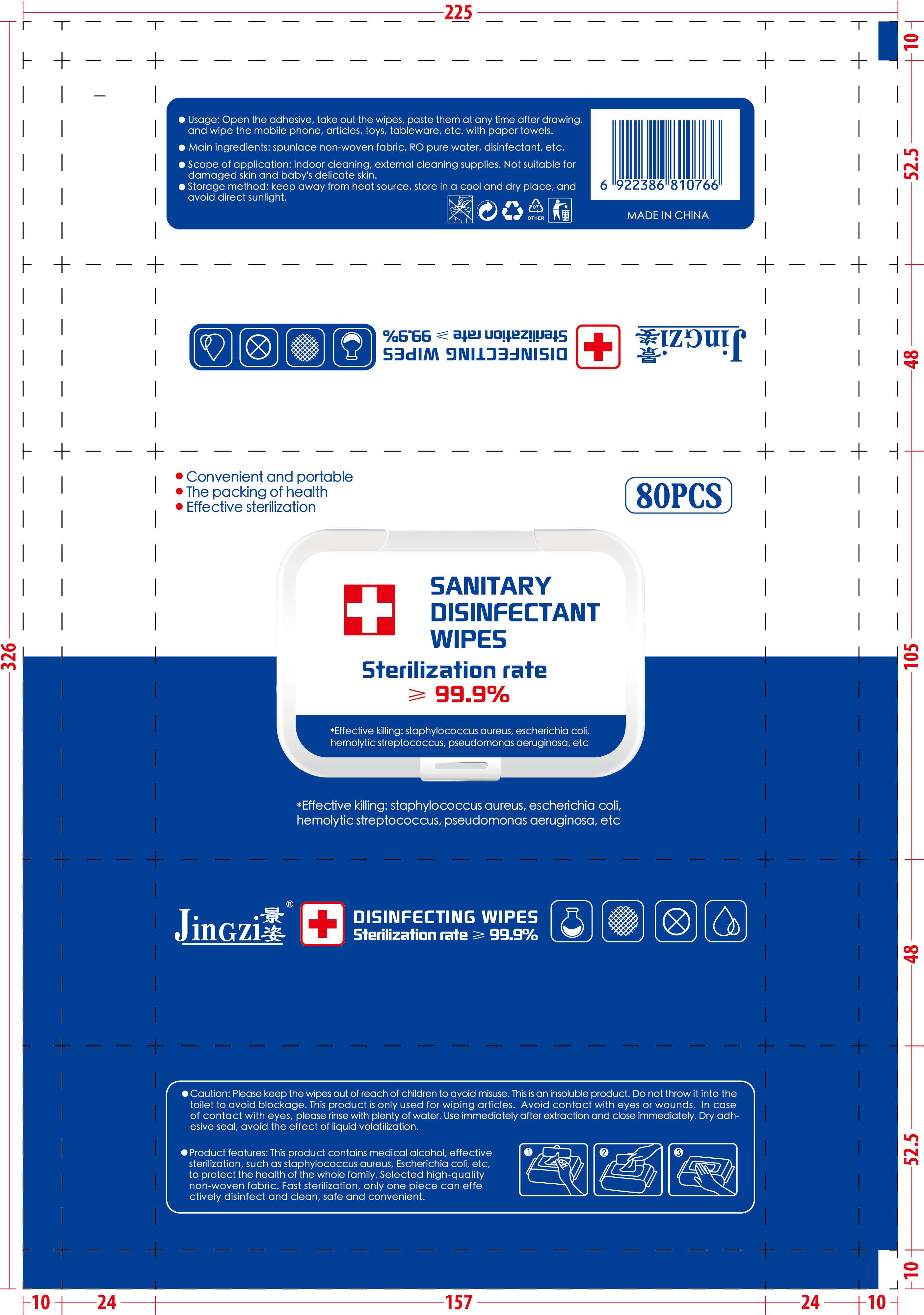 DRUG LABEL: Sanitary alcohol disinfectant wipes
NDC: 41425-001 | Form: CLOTH
Manufacturer: Yiwu Aojie Maternal And Infant Products Co., Ltd
Category: otc | Type: HUMAN OTC DRUG LABEL
Date: 20200519

ACTIVE INGREDIENTS: PROPYLENE GLYCOL 1.98 g/80 1; ALCOHOL 202.5 mL/80 1; BENZALKONIUM CHLORIDE 2.475 g/80 1; METHYLISOTHIAZOLINONE 5.85 mg/80 1; PHENOXYETHANOL 0.44491 g/80 1
INACTIVE INGREDIENTS: WATER

DOSAGE AND ADMINISTRATION

keep away from heat source, store in a cool and dry place, and avoid direct sunlight.

INACTIVE INGREDIENT

pure water

INDICATIONS AND USAGE

Open the adhesive, take out the wipes, paste them at any time after drawing,and wipe the mobile phone, articles, toys, tableware, etc. with paper towels.

ACTIVE INGREDIENT

alcohol

Benzalkamine

2-methyl-4-isothiazoline-3-one

propylene glycol

2-phenoxyethanol

keep out of reach of children

PURPOSE

Disinfection
Sterilization
No Rinseing

WARNINGS

Please keep the wipes out of reach of children to avoid misuse. This is an insoluble product. Do not throw it into the toilet to avoid blockage. This product is only used for wiping articles. Avoid contact with eyes or wounds. In case of contact with eyes, please rinse with plenty of water. Use immediately after extraction and close immediately. Dry adh-esive seal, avoid the effect of liquid volatilization.